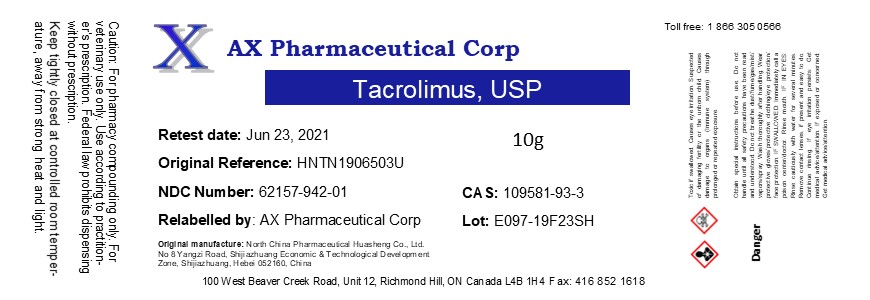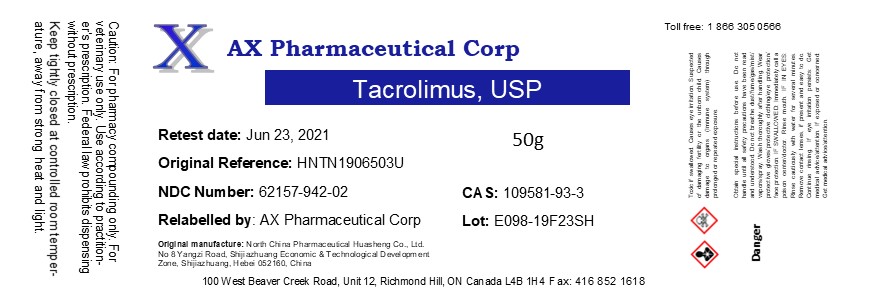 DRUG LABEL: Tacrolimus
NDC: 62157-942 | Form: POWDER
Manufacturer: AX Pharmaceutical Corp
Category: other | Type: BULK INGREDIENT
Date: 20191210

ACTIVE INGREDIENTS: TACROLIMUS 1 g/1 g

Tacrolimus